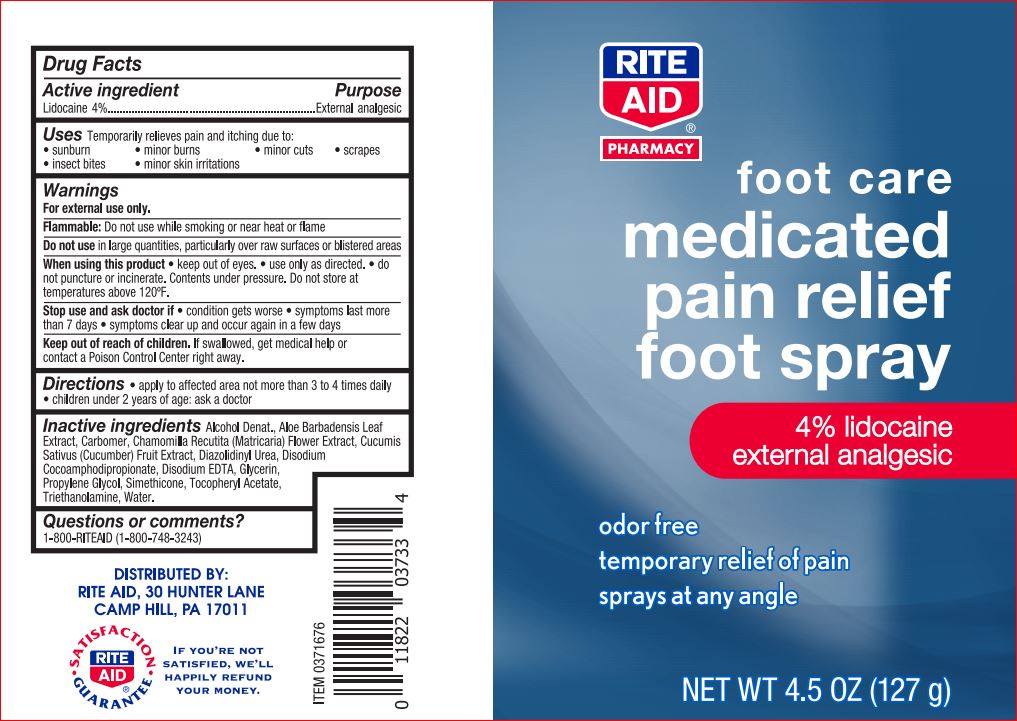 DRUG LABEL: Medicated Pain Relief Foot
NDC: 11822-7799 | Form: SPRAY
Manufacturer: Rite Aid
Category: otc | Type: HUMAN OTC DRUG LABEL
Date: 20180529

ACTIVE INGREDIENTS: Lidocaine 4 g/100 mL
INACTIVE INGREDIENTS: Alcohol; ALOE VERA LEAF; CHAMOMILE; CUCUMBER; Diazolidinyl Urea; Disodium Cocoamphodipropionate; EDETATE DISODIUM; Glycerin; Propylene Glycol; .ALPHA.-TOCOPHEROL ACETATE; TROLAMINE; Water

Drug Facts

Active ingredient Purpose
Lidocaine 4%................................................................External analgesic

Uses

Temporarily relieves pain and itching due to: • sunburn • minor burns • minor cuts • scrapes • insect bites • minor skin irritations

Warnings For external use only.

Flammable: Do not use while smoking or near heat or flame Do not use in large quantities, particularly over raw surfaces or blistered areas
When using this product
• keep out of eyes
• use only as directed.
• do not puncture or incinerate. Contents under pressure. Do not store at temperatures above 120ºF.
Stop use and ask doctor if
• condition gets worse • symptoms last more than 7 days
• symptoms clear up and occur again in a few days

Keep out of reach of children. If swallowed, get medical help or contact a Poison Control Center right away

DOSAGE AND ADMINISTRATION

Directions • adults and children 2 years of age and older: apply to affected area not more than 3 to 4 times daily • children under 2 years of age: ask a doctor • to apply to face, spray into palm of hand and gently apply

Inactive ingredients

Alcohol Denat.
Aloe Barbadensis Leaf Extract
Carbomer
Chamomilla Recutita (Matricaria) Flower Extract
Cucumis Sativus (Cucumber) Fruit Extract
Diazolidinyl Urea
Disodium Cocoamphodipropionate
Disodium EDTA
Glycerin
Propylene Glycol
Simethicone
Tocopheryl Acetate
Triethanolamine
Water